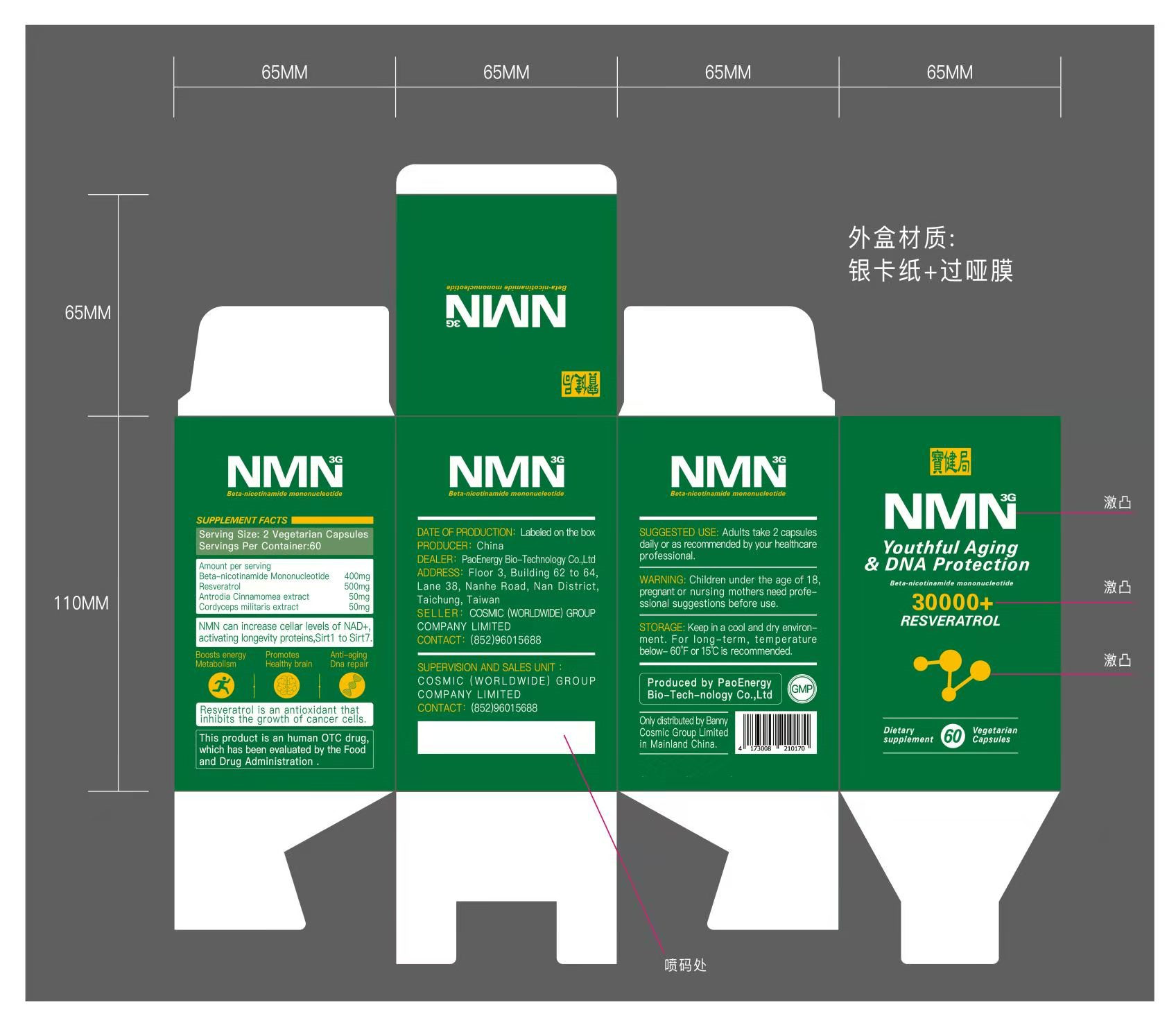 DRUG LABEL: NMN
NDC: 86342-003 | Form: CAPSULE
Manufacturer: Cosmic (Worldwide) Group Company Limited
Category: homeopathic | Type: HUMAN OTC DRUG LABEL
Date: 20210909

ACTIVE INGREDIENTS: RESVERATROL 30 g/60 1; NICOTINAMIDE RIBOTIDE 24 g/60 1
INACTIVE INGREDIENTS: CORDYCEPS MILITARIS WHOLE; TAIWANOFUNGUS CAMPHORATUS WHOLE

INDICATIONS AND USAGE

Resveratrol is an antioxidant thatinhibits the growth of cancer cells.This product is an human OTC drug,which has been evaluated by the Foodand Drug Administration .

SUGGESTED USE

Adults take 2 capsulesdaily or as recommended by your healthcare professional.

INACTIVE INGREDIENT

Antrodia Cinnamomea extract
Cordyceps militaris extract

STORAGE

Keep in a cool and dry environment. For long-term, temperaturebelow-60°F or 15°C is recommended.

ACTIVE INGREDIENT

Beta-nicotinamide Mononucleotide
Resveratrol

PURPOSE

NMN can increase cellar levels of NAD+,activating longevity proteins,Sirt1 to Sirt7.
Bocsts energy Metabollsm
Promotes Heaithy brain
Anti-aging Dna repair

Keep out of reach of children

WARNINGS

Children under the age of 18,pregnant or nursing mothers need professional suggestions before use.